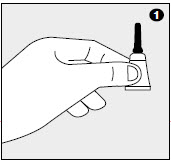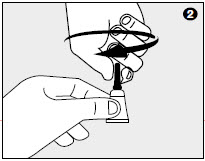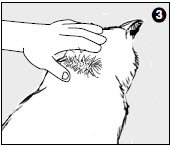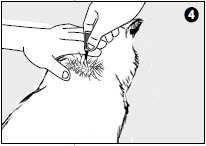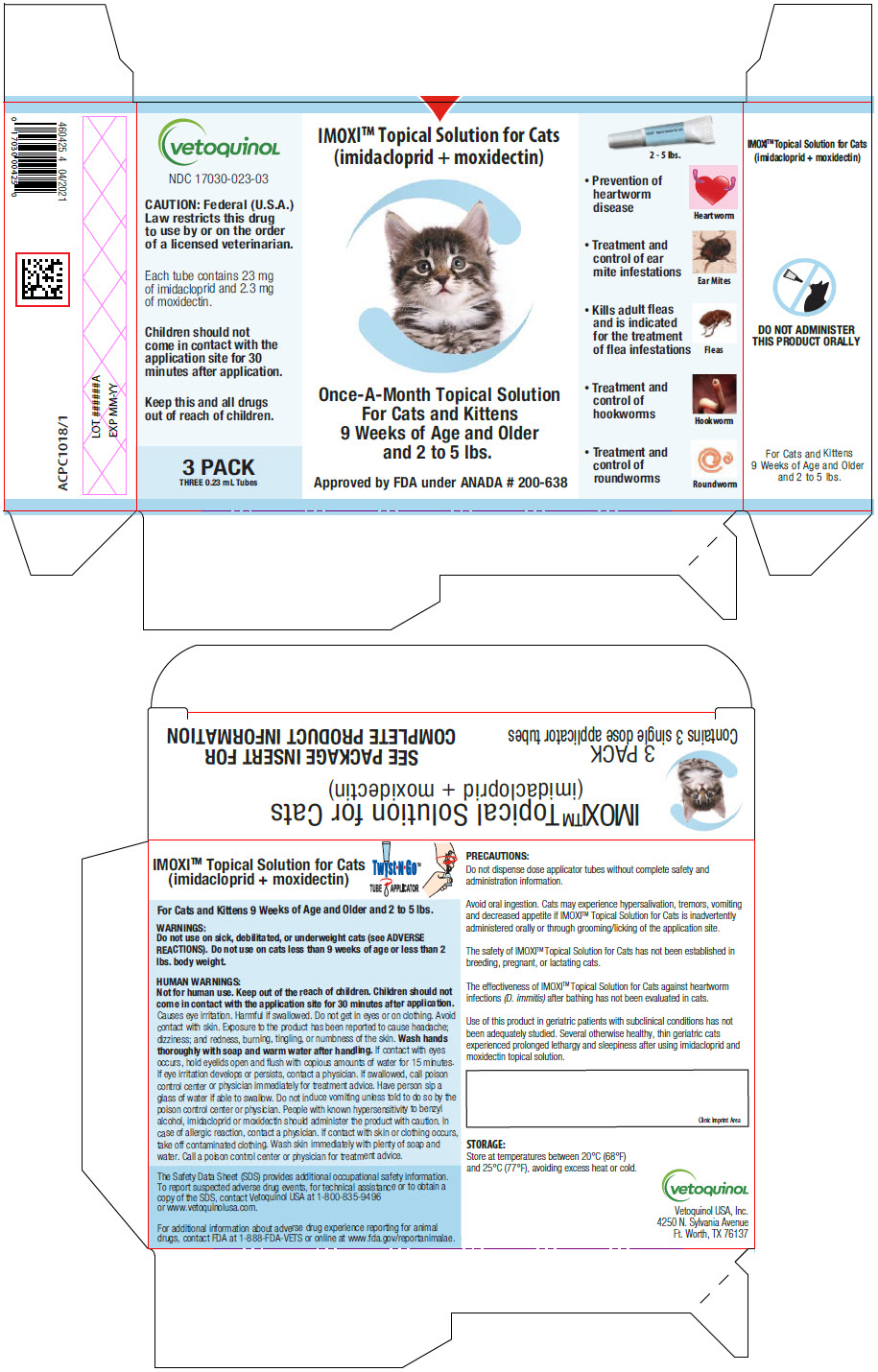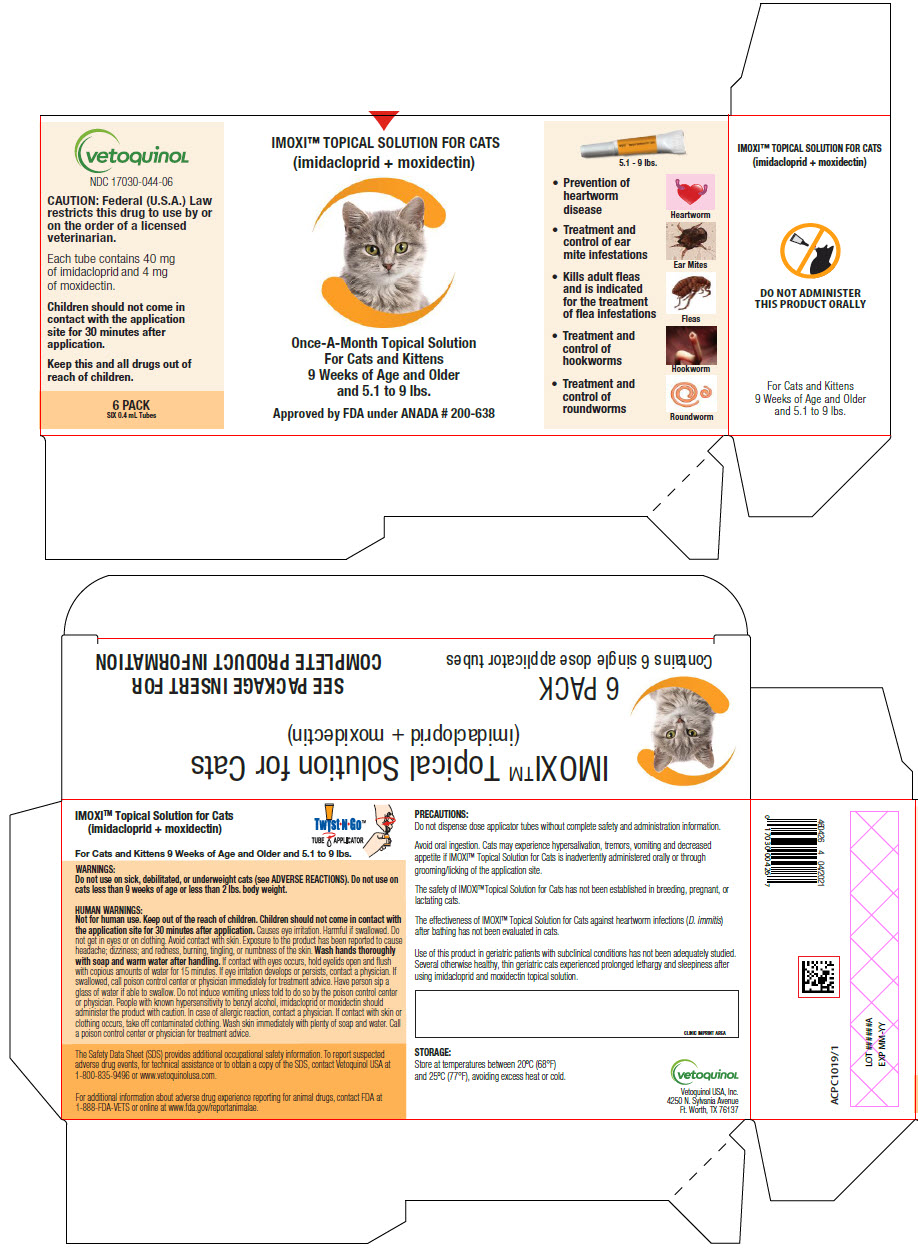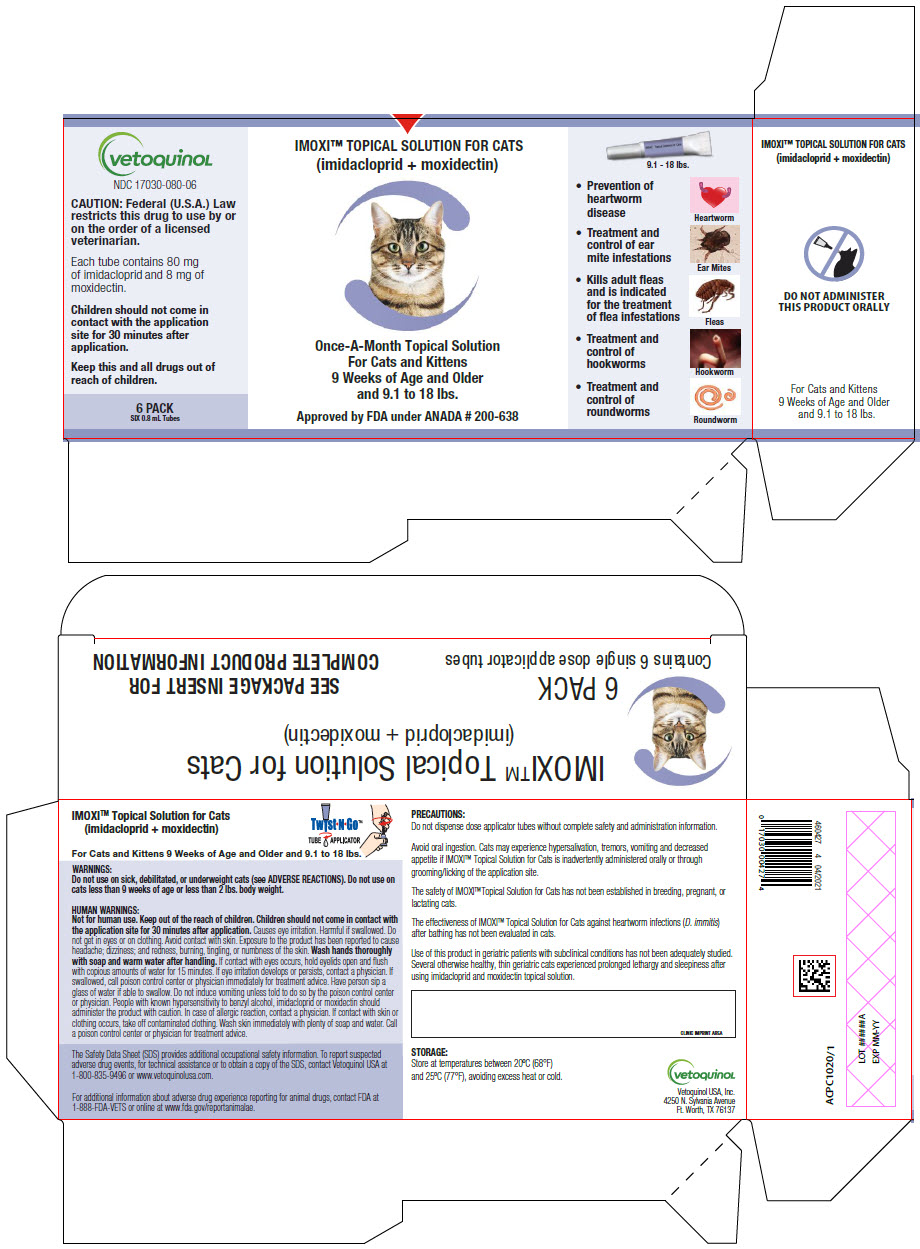 DRUG LABEL: IMOXI 
NDC: 17030-023 | Form: SOLUTION
Manufacturer: Vetoquinol USA, Inc.
Category: animal | Type: PRESCRIPTION ANIMAL DRUG LABEL
Date: 20221213

ACTIVE INGREDIENTS: IMIDACLOPRID 100 mg/1 mL; MOXIDECTIN 10 mg/1 mL

IMOXI™ Topical Solution for Cats
(imidacloprid + moxidectin)

VETERINARY INDICATIONS

Once-a-month topical solution for cats for the prevention of heartworm disease, kills adult fleas, is indicated for the treatment of flea infestations, as well as the treatment and control of ear mite infestations and intestinal parasite infections in cats and kittens 9 weeks of age and older and that weigh at least 2 lbs.

CAUTION:

Federal (U.S.A.) Law restricts this drug to use by or on the order of a licensed veterinarian.

DESCRIPTION:

IMOXI™ Topical Solution for Cats (10% imidacloprid + 1% moxidectin) is a colorless to yellow ready-to-use solution packaged in single-dose applicator tubes for topical treatment of cats. The formulation and dosage schedule are designed to provide a minimum of 4.5 mg/lb (10.0 mg/kg) imidacloprid and 0.45 mg/lb (1.0 mg/kg) moxidectin based on body weight.

Imidacloprid is a chloronicotinyl nitroguanidine insecticide. The chemical name of imidacloprid is 1-[(6-Chloro-3-pyridinyl)methyl]-N-nitro-2-imidazolidinimine. Moxidectin is a semisynthetic macrocyclic lactone endectocide derived from the actinomycete Streptomycetes cyaneogriseus noncyanogenus. The chemical name of moxidectin is [6R, 23E, 25S(E)]-5-O-Demethyl-28-deoxy-25- (1,3-dimethyl-1-butenyl)-6,28-epoxy-23-(methoxyimino) milbemycin B.

INDICATIONS:

IMOXI™ Topical Solution for Cats is indicated for the prevention of heartworm disease caused by Dirofilaria immitis. IMOXI™ Topical Solution for Cats kills adult fleas (Ctenocephalides felis) and is indicated for the treatment of flea infestations. IMOXI™ Topical Solution for Cats is also indicated for the treatment and control of ear mite (Otodectes cynotis) infestations and the following intestinal parasites:

Intestinal Parasite |  | Intestinal Stage
Intestinal Parasite |  | Adult | Immature Adult | Fourth Stage Larvae
Hookworm Species | Ancylostoma tubaeforme | X | X | X
Roundworm Species | Toxocara cati | X |  | X

WARNINGS:

Do not use on sick, debilitated, or underweight cats (see ADVERSE REACTIONS). Do not use on cats less than 9 weeks of age or less than 2 lbs. body weight.

SAFE HANDLING WARNING

HUMAN WARNINGS:

Not for human use. Keep out of the reach of children.

Children should not come in contact with the application site for 30 minutes after application.

Causes eye irritation. Harmful if swallowed. Do not get in eyes or on clothing. Avoid contact with skin. Exposure to the product has been reported to cause headache; dizziness; and redness, burning, tingling, or numbness of the skin. Wash hands thoroughly with soap and warm water after handling. If contact with eyes occurs, hold eyelids open and flush with copious amounts of water for 15 minutes. If eye irritation develops or persists, contact a physician. If swallowed, call poison control center or physician immediately for treatment advice. Have person sip a glass of water if able to swallow. Do not induce vomiting unless told to do so by the poison control center or physician. People with known hypersensitivity to benzyl alcohol, imidacloprid or moxidectin should administer the product with caution. In case of allergic reaction, contact a physician. If contact with skin or clothing occurs, take off contaminated clothing. Wash skin immediately with plenty of soap and water. Call a poison control center or physician for treatment advice.

The Safety Data Sheet (SDS) provides additional occupational safety information. To report suspected adverse drug events, for technical assistance or to obtain a copy of the SDS, contact Vetoquinol USA at 1-800-835-9496 or www.vetoquinolusa.com.

For additional information about adverse drug experience reporting for animal drugs, contact FDA at 1-888-FDA-VETS or online at www.fda.gov/reportanimalae.

PRECAUTIONS:

Do not dispense dose applicator tubes without complete safety and administration information.

Avoid oral ingestion. Cats may experience hypersalivation, tremors, vomiting and decreased appetite if IMOXI™ Topical Solution for Cats is inadvertently administered orally or through grooming/licking of the application site.

The safety of IMOXI™ Topical Solution for Cats has not been established in breeding, pregnant, or lactating cats.

The effectiveness of IMOXI™ Topical Solution for Cats against heartworm infections (D. immitis) after bathing has not been evaluated in cats.

Use of this product in geriatric patients with subclinical conditions has not been adequately studied. Several otherwise healthy, thin geriatric cats experienced prolonged lethargy and sleepiness after using imidacloprid and moxidectin topical solution. (See ADVERSE REACTIONS).

ADVERSE REACTIONS:

Field Study: Following treatment with imidacloprid and moxidectin topical solution or an active control, cat owners reported the following post-treatment reactions:

OBSERVATION | Imidacloprid and Moxidectin Topical Solution n=113 | Active Control n=38
Lethargy (protracted sleeping, poorly responsive) | 3 cats [These three cats were from the same household and included one 13-yr-old cat in good health, one 15-yr-old FIV positive cat in good health, and one 15-yr-old, underweight cat in fair health. Lethargy was noted for 24 to 36 hrs after the first treatment only; one cat was unsteady at 48hrs. These cats were not on other medications.] (2.7%) | None observed
Behavioral changes (e.g., agitated, excessive grooming, hiding, pacing, spinning) | 9 cats (8.0%) | 1 cat (2.6%)
Discomfort (e.g., scratching, rubbing, head-shaking) | 5 cats (4.4%) | None observed
Hypersalivation (within 1 hour after treatment) | 3 cats (2.7%) | None observed
Polydipsia | 3 cats (2.7%) | None observed
Coughing and gagging | 1 cat (0.9%) | None observed

During another field study, a 16-year-old cat with renal disease slept in the same place without moving for two days following application. (See PRECAUTIONS).

Laboratory Effectiveness Studies: Imidacloprid and moxidectin topical solution was administered at the recommended dose to 215 cats in 20 effectiveness studies. One random-sourced cat exhibited signs consistent with either moxidectin toxicity or viral respiratory disease and died 26 hours after product application; necropsy findings were inconclusive as to the cause of death. A second cat that became ill 3 days after application of imidacloprid and moxidectin topical solution responded to treatment for respiratory infection and completed the study. A third cat became ill on day 3 and died with signs and lesions attributable to panleukopenia on day 7 after moxidectin application.

Post-Approval Experience: The following adverse events are based on post-approval adverse drug experience reporting. Not all adverse reactions are reported to FDA CVM. It is not always possible to reliably estimate the adverse event frequency or establish a causal relationship to product exposure using this data. The following adverse events in cats are listed in decreasing order of reporting frequency: hypersalivation, depression/lethargy, application site reactions (alopecia, pruritus, lesions, and erythema), decreased appetite, vomiting, hyperactivity, ataxia, trembling, and behavior disorder (hiding).

In some cases, death has been reported. In humans, ocular and dermal irritation, nausea, numbness or tingling of the mouth and lips, anaphylaxis, pruritus, vomiting, and tongue/taste abnormalities have been reported following exposure to imidacloprid and moxidectin topical solution.

To report suspected adverse drug events, for technical assistance or to obtain a copy of the SDS, contact Vetoquinol USA at 1-800-835-9496 or www.vetoquinolusa.com.

For additional information about adverse drug experience reporting for animal drugs, contact FDA at 1-888-FDA-VETS or online at www.fda.gov/reportanimalae.

DOSAGE AND ADMINISTRATION:

The recommended minimum dose is 4.5 mg/lb (10.0 mg/kg) imidacloprid and 0.45 mg/lb (1.0 mg/kg) moxidectin, once a month, by topical administration.

Do not apply to irritated skin.

1. Remove one dose applicator tube from the package. As specified in the following table, administer the entire contents of the IMOXI™ Topical Solution for Cats tube that correctly corresponds with the body weight of the cat.

Cat (lbs.) | Volume (mL) | Imidacloprid (mg) | Moxidectin (mg)
2-5 | 0.23 | 23 | 2.3
5.1-9 | 0.4 | 40 | 4
9.1-18 [Cats over 18 lbs. should be treated with the appropriate combination of IMOXI™ Topical Solution for Cats tubes.] | 0.8 | 80 | 8

2. While holding the Twist•N•Go™ tube in an upright position, twist dispensing tip clockwise about ½ turn to break the tube's seal. Remove the cap from the tube.

3. Part the hair on the back of the cat's neck at the base of the head, until the skin is visible.

4. Place the tip of the tube on the skin and apply the entire contents directly on the exposed skin. Lift the tube away from the skin before releasing pressure on the tube.

Do not get this product in the cat's mouth or eyes or allow the cat to lick the application site for 30 minutes. Treatment at the base of the head will minimize the opportunity for ingestion by grooming. In households with multiple pets, keep animals separated to prevent licking of the application site.

Stiff, matted hair or a damp, oily appearance of the hair may be observed at the application site on some cats. This is temporary and does not affect the safety and effectiveness of the product.

Heartworm Prevention: For prevention of heartworm disease, IMOXI™ Topical Solution for Cats should be administered at one-month intervals. IMOXI™ Topical Solution for Cats may be administered year-around or at a minimum should start one month before the first expected exposure to mosquitoes and should continue at monthly intervals until one month after the last exposure to mosquitoes. If a dose is missed and a 30-day interval between doses is exceeded, administer IMOXI™ Topical Solution for Cats immediately and resume the monthly dosing schedule. When replacing another heartworm preventative product in a heartworm prevention program, the first treatment with IMOXI™ Topical Solution for Cats should be given within one month of the last dose of the former medication. At the discretion of the veterinarian, cats older than 6 months of age may be tested to determine the presence of existing heartworm infection before treatment with IMOXI™ Topical Solution for Cats. (See ADVERSE REACTIONS – Post-Approval Experience).

Flea Treatment: For the treatment of flea infestations, IMOXI™ Topical Solution for Cats should be administered at one-month intervals. If the cat is already infested with fleas when the first dose of IMOXI™ Topical Solution for Cats is administered, adult fleas on the cat will be killed. However, re-infestation from the emergence of pre-existing pupae in the environment may continue to occur for six weeks or longer after treatment is initiated. Cats treated with imidacloprid, including those with pre-existing flea allergy dermatitis, have shown clinical improvement as a direct result of elimination of fleas from the cat.

Ear Mite Treatment: For the treatment of ear mites (Otodectes cynotis), IMOXI™ Topical Solution for Cats should be administered once as a single topical dose. Monthly use of IMOXI™ Topical Solution for Cats will control any subsequent ear mite infestations.

Intestinal Nematode Treatment: For the treatment and control of intestinal hookworm infections caused by Ancylostoma tubaeforme (adults, immature adults and fourth stage larvae) and roundworm infections caused by Toxocara cati (adults and fourth stage larvae), IMOXI™ Topical Solution for Cats should be administered once as a single topical dose.

ANIMAL SAFETY:

Studies in Kittens: Imidacloprid and moxidectin topical solution was topically applied at 0, 1, 3, and 5× the maximum dose to 48 healthy 9-week-old kittens on days 0, 28, and 56. Lethargy was observed in 1 kitten from the 3× group and 1 from the 5× group on the day after initial treatment; the kitten from the 3× group was also disoriented and ataxic. One kitten from the 3× group had a slow pupillary light response two days after treatment and one had tremors the day after treatment. Hypersalivation was seen in one kitten from the 5× group approximately six hours post-treatment. One kitten from the 3× group was scratching at the treatment site 2 days after treatment. Slight cough was noted in 7 different kittens (2-0×, 2-1×, and 3-5×) during the 13-day period following the first treatment. Histopathology showed granulomatous inflammation at the treatment site in three 1× kittens. Causal relationship to the drug could not be determined. Pulmonary inflammation (1-5×) and lymphoid hyperplasia (2-1×, 4-3×) were seen in treated kittens. In a second study, imidacloprid and moxidectin topical solution was topically applied at 0, 1.7, 5.2 and 8.7× the maximum dose to 48 healthy 9-week-old kittens every two weeks for 6 doses. One kitten in the 8.7× group apparently ingested an unknown amount of the drug and developed the following clinical signs prior to euthanasia: mydriasis, salivation, depression, vomiting, unsteadiness, rapid to slow to difficult breathing, poor pupillary response, generalized tremors, inability to move, and nystagmus. Two kittens in the 5.2× group developed mydriasis, salivation, depression, squinting, and poor appetite. A kitten in the 1.7× group developed mydriasis.

Dose Tolerance Study: Eight healthy juvenile cats were topically dosed with a single application of imidacloprid and moxidectin topical solution at 10 times the recommended dose volume. Mild, transient hypersalivation occurred in two of the cats.

Oral Study in Cats: The oral safety of imidacloprid and moxidectin topical solution was tested in case of accidental oral ingestion. The maximum topical dose was orally administered to twelve healthy 9-week-old kittens. Hypersalivation (8 of 12 kittens) and vomiting (12 of 12 kittens) were observed immediately post-treatment. Tremors developed in one kitten within 1 hour, resolving without treatment within the next hour. All 12 kittens were either anorexic or had decreased appetite for at least 1 day following treatment. In 3 kittens, the anorexia or decreased appetite continued into the second week following treatment. There was a post-treatment loss of body weight in treated kittens compared to control kittens. In a pilot safety study using kittens younger in age and lighter in weight than allowed by product labeling, an 8-week-old kitten weighing 0.6 kg orally received 2× of the label topical dose (0.46 mL/kg). Immediately after dosing, it vomited, had labored breathing and slight tremors. Within 4 hours, it was normal, but was found dead on day 6. Necropsy could not determine the cause of death.

Study in Heartworm Positive Cats: Young adult cats were inoculated subcutaneously with third-stage D. immitis larvae. At 243-245 days post-infection, immunoserology and echocardiography were performed to identify cats with adult heartworm burdens similar to naturally-acquired infections. Two groups were treated topically with either imidacloprid and moxidectin topical solution at the label dose or placebo, once every 28 days, for three consecutive treatments. A third group was treated topically, once, with imidacloprid and moxidectin topical solution at 5× the label dose. Sporadic vomiting and labored breathing related to heartworm burden were observed in the treatment and control groups. There was no difference between treatment groups in the numbers of adult D. immitis recovered at study conclusion. No adverse reactions were associated with the topical application of imidacloprid and moxidectin topical solution to experimentally heartworm-infected cats.

STORAGE INFORMATION:

Store at temperatures between 20°C (68°F) and 25°C (77°F), avoiding excess heat or cold.

HOW SUPPLIED:

Applications Per Package

3 × 0.23 mL tubes

6 × 0.4 mL tubes

6 × 0.8 mL tubes

Approved by FDA under ANADA # 200-638

Made in U.S.A. © 2020 Vetoquinol USA, Inc.
Vetoquinol, the Vetoquinol logo, and
IMOXI™ Topical Solution for Cats are registered
trademarks of Vetoquinol USA, Inc.

R2 - 08/2020

ACPX1012

Vetoquinol USA, Inc.
4250 N. Sylvania Avenue
Ft. Worth, TX 76137

PRINCIPAL DISPLAY PANEL - 0.23 mL Tube Blister Pack Carton

vetoquinol

NDC 17030-023-03

CAUTION: Federal (U.S.A.)
Law restricts this drug
to use by or on the order
of a licensed veterinarian.

Each tube contains 23 mg
of imidacloprid and 2.3 mg
of moxidectin.

Children should not
come in contact with the
application site for 30
minutes after application.

Keep this and all drugs
out of reach of children.

3 PACK
THREE 0.23 mL Tubes

IMOXI™ Topical Solution for Cats
(imidacloprid + moxidectin)

Once-A-Month Topical Solution
For Cats and Kittens
9 Weeks of Age and Older
and 2 to 5 lbs.

Approved by FDA under ANADA # 200-638

2 - 5 lbs.

- Prevention of
  heartworm
  disease
- Treatment and
  control of ear
  mite infestations
- Kills adult fleas
  and is indicated
  for the treatment
  of flea infestations
- Treatment and
  control of
  hookworms
- Treatment and
  control of
  roundworms

PRINCIPAL DISPLAY PANEL - 0.4 mL Tube Blister Pack Carton

vetoquinol

NDC 17030-044-06

CAUTION: Federal (U.S.A.) Law
restricts this drug to use by or
on the order of a licensed
veterinarian.

Each tube contains 40 mg
of imidacloprid and 4 mg
of moxidectin.

Children should not come in
contact with the application
site for 30 minutes after
application.

Keep this and all drugs out of
reach of children.

6 PACK
SIX 0.4 mL Tubes

IMOXI™ TOPICAL SOLUTION FOR CATS
(imidacloprid + moxidectin)

Once-A-Month Topical Solution
For Cats and Kittens
9 Weeks of Age and Older
and 5.1 to 9 lbs.

Approved by FDA under ANADA # 200-638

5.1 - 9 lbs.

- Prevention of
  heartworm
  disease
- Treatment and
  control of ear
  mite infestations
- Kills adult fleas
  and is indicated
  for the treatment
  of flea infestations
- Treatment and
  control of
  hookworms
- Treatment and
  control of
  roundworms

PRINCIPAL DISPLAY PANEL - 0.8 mL Tube Blister Pack Carton

vetoquinol

NDC 17030-080-06

CAUTION: Federal (U.S.A.) Law
restricts this drug to use by or
on the order of a licensed
veterinarian.

Each tube contains 80 mg
of imidacloprid and 8 mg of
moxidectin.

Children should not come in
contact with the application
site for 30 minutes after
application.

Keep this and all drugs out of
reach of children.

6 PACK
SIX 0.8 mL Tubes

IMOXI™ TOPICAL SOLUTION FOR CATS
(imidacloprid + moxidectin)

Once-A-Month Topical Solution
For Cats and Kittens
9 Weeks of Age and Older
and 9.1 to 18 lbs.

Approved by FDA under ANADA # 200-638

9.1 - 18 lbs.

- Prevention of
  heartworm
  disease
- Treatment and
  control of ear
  mite infestations
- Kills adult fleas
  and is indicated
  for the treatment
  of flea infestations
- Treatment and
  control of
  hookworms
- Treatment and
  control of
  roundworms